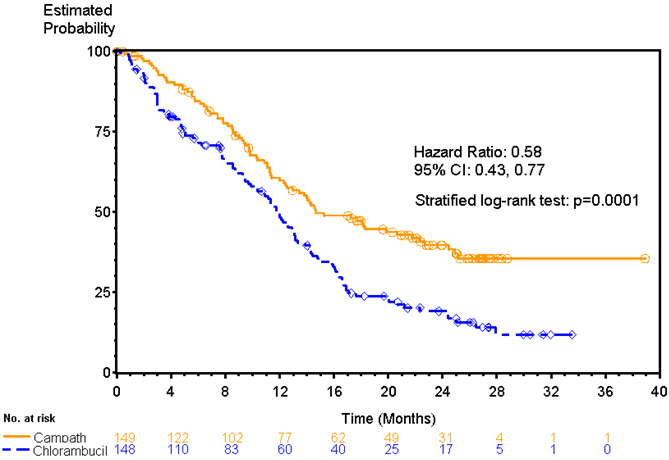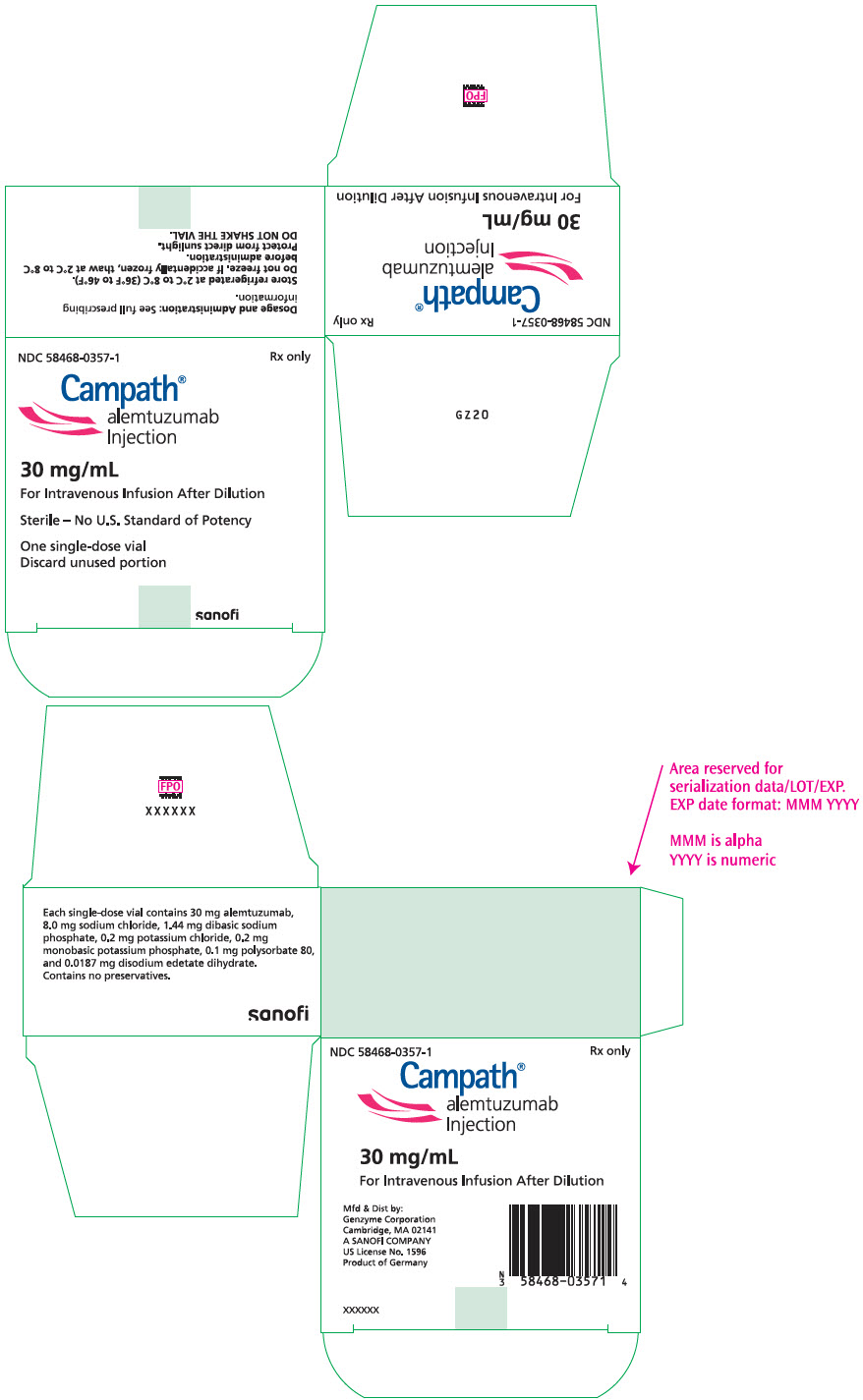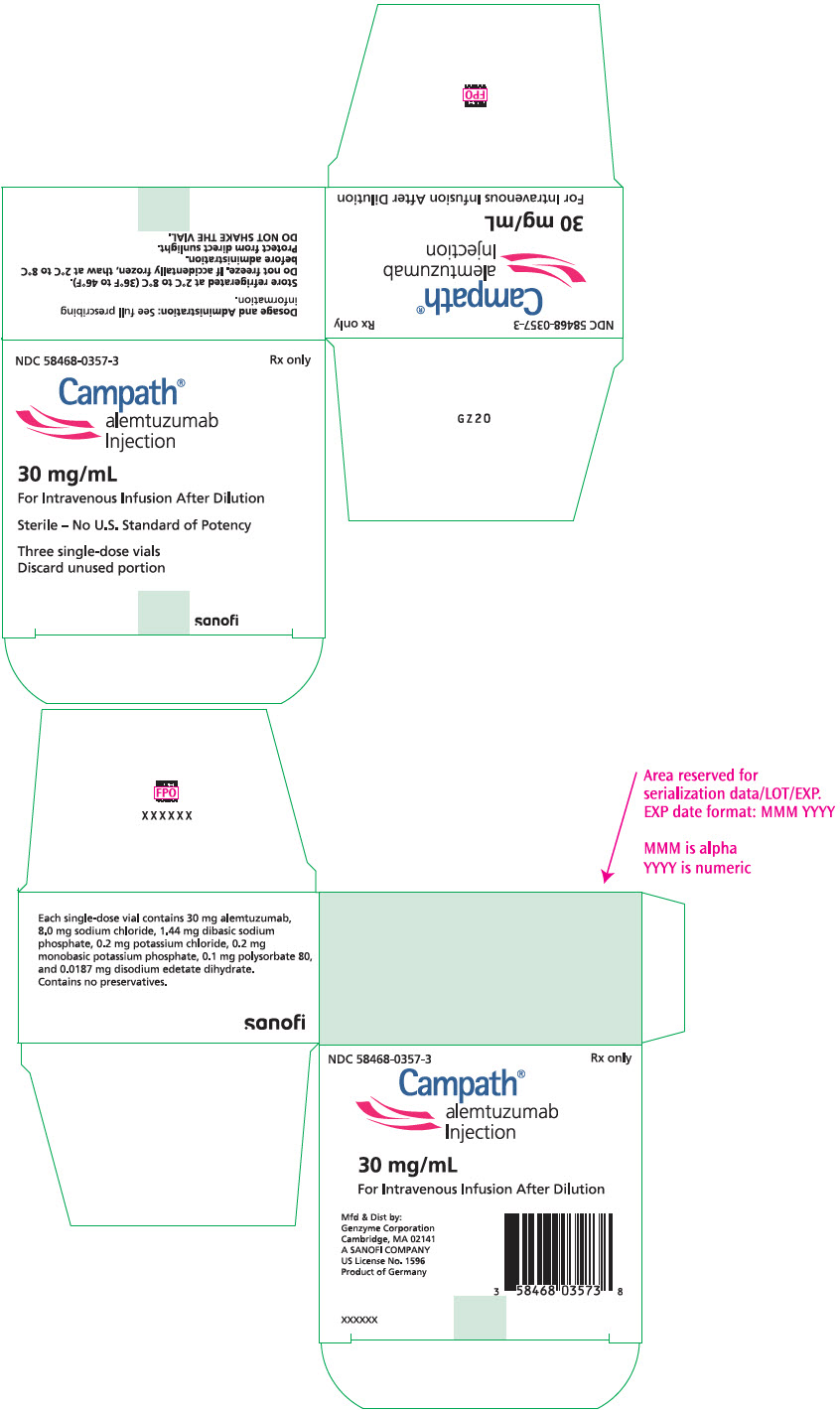 DRUG LABEL: Campath
NDC: 58468-0357 | Form: INJECTION
Manufacturer: Genzyme Corporation
Category: prescription | Type: HUMAN PRESCRIPTION DRUG LABEL
Date: 20251105

ACTIVE INGREDIENTS: ALEMTUZUMAB 30 mg/1 mL
INACTIVE INGREDIENTS: SODIUM CHLORIDE 8 mg/1 mL; SODIUM PHOSPHATE, DIBASIC, UNSPECIFIED FORM 1.44 mg/1 mL; POTASSIUM CHLORIDE 0.2 mg/1 mL; MONOBASIC POTASSIUM PHOSPHATE 0.2 mg/1 mL; POLYSORBATE 80 0.1 mg/1 mL; EDETATE DISODIUM 0.0187 mg/1 mL

HIGHLIGHTS OF PRESCRIBING INFORMATION

These highlights do not include all the information needed to use CAMPATH safely and effectively. See full prescribing information for CAMPATH.
CAMPATH® (alemtuzumab) injection, for intravenous use
Initial U.S. Approval: 2001

WARNING: CYTOPENIAS, INFUSION-RELATED REACTIONS, AND INFECTIONS

See full prescribing information for complete boxed warning.

Serious, including fatal, cytopenias, infusion-related reactions, and infections can occur (5.1–5.3).

- Limit doses to 30 mg (single) and 90 mg (cumulative weekly); higher doses increase risk of pancytopenia. (2.1)
- Escalate dose gradually and monitor patients during infusion. Withhold therapy for Grade 3 or 4 infusion-related reactions. (5.2)
- Administer prophylaxis against Pneumocystis jirovecii pneumonia (PCP) and herpes virus infections. (2.2, 5.3)

1 INDICATIONS AND USAGE

CAMPATH is a CD52-directed cytolytic antibody indicated as a single agent for the treatment of B-cell chronic lymphocytic leukemia (B-CLL). (1)

2 DOSAGE AND ADMINISTRATION

- Administer as an intravenous infusion over 2 hours. (2.1)
- Escalate to recommended dose of 30 mg/day three times per week for 12 weeks. (2.1)
- Premedicate with oral antihistamine and acetaminophen. (2.2)

3 DOSAGE FORMS AND STRENGTHS

Injection: 30 mg/1 mL single-dose vial (3)

4 CONTRAINDICATIONS

None (4)

5 WARNINGS AND PRECAUTIONS

- Cytopenias: Obtain complete blood counts (CBC) and platelet counts at weekly intervals during therapy and CD4 counts after therapy until recovery to ≥200 cells/µL. Withhold for severe cytopenias. Discontinue for autoimmune or severe hematologic adverse reactions. (2.2, 5.1)
- Immunosuppression/Infections: CAMPATH induces severe and prolonged lymphopenia and increases risk of infection. If a serious infection occurs, withhold treatment until infection resolves. (5.3)
- Immunization: Do not administer live viral vaccines to patients who have recently received CAMPATH. (5.4)

6 ADVERSE REACTIONS

Most common adverse reactions (≥10%): cytopenias, infusion-related reactions, cytomegalovirus (CMV) and other infections, nausea, emesis, diarrhea, and insomnia. (6)

To report SUSPECTED ADVERSE REACTIONS, contact Genzyme Corporation at 1-877-4-CAMPATH (1-877-422-6728) or FDA at 1-800-FDA-1088 or www.fda.gov/medwatch.

8 USE IN SPECIFIC POPULATIONS

- Pregnancy: May cause fetal harm. (8.1)
- Lactation: Advise not to breastfeed. (8.2)

FULL PRESCRIBING INFORMATION

WARNING: CYTOPENIAS, INFUSION-RELATED REACTIONS, AND INFECTIONS

Cytopenias: Serious, including fatal, pancytopenia/marrow hypoplasia, autoimmune idiopathic thrombocytopenia, and autoimmune hemolytic anemia can occur in patients receiving CAMPATH. Single doses of CAMPATH greater than 30 mg or cumulative doses greater than 90 mg per week increase the incidence of pancytopenia [see Warnings and Precautions (5.1)].

Infusion-Related Reactions: CAMPATH administration can result in serious, including fatal, infusion-related reactions. Carefully monitor patients during infusions and withhold CAMPATH for Grade 3 or 4 infusion-related reactions. Gradually escalate CAMPATH to the recommended dose at the initiation of therapy and after interruption of therapy for 7 or more days [see Dosage and Administration (2.1) and Warnings and Precautions (5.2)].

Immunosuppression/Infections: Serious, including fatal, bacterial, viral, fungal, and protozoan infections can occur in patients receiving CAMPATH. Administer prophylaxis against Pneumocystis jirovecii pneumonia (PCP) and herpes virus infections [see Dosage and Administration (2.2) and Warnings and Precautions (5.3)].

1 INDICATIONS AND USAGE

CAMPATH is indicated as a single agent for the treatment of B-cell chronic lymphocytic leukemia (B-CLL).

2 DOSAGE AND ADMINISTRATION

2.1 Dosing Schedule and Administration

- Administer as an intravenous infusion over 2 hours. Do not administer as intravenous push or bolus.
- Recommended Dosing Regimen
  - Gradually escalate to the maximum recommended single dose of 30 mg. Escalation is required at initiation of dosing or if dosing is held ≥7 days during treatment. Escalation to 30 mg ordinarily can be accomplished in 3 to 7 days.
  - Escalation Strategy:
    - Administer 3 mg daily until infusion-related reactions are ≤ Grade 2 [see Adverse Reactions (6.1)].
    - Then administer 10 mg daily until infusion-related reactions are ≤ Grade 2.
    - Then administer 30 mg/day three times per week on alternate days (e.g., Mon-Wed-Fri). The total duration of therapy, including dose escalation, is 12 weeks.
- Single doses of greater than 30 mg or cumulative doses greater than 90 mg per week increase the incidence of pancytopenia.

2.2 Recommended Concomitant Medications

- Premedicate with diphenhydramine (50 mg) and acetaminophen (500–1000 mg) 30 minutes prior to first infusion and each dose escalation. Institute appropriate medical management (e.g., glucocorticoids, epinephrine, meperidine) for infusion-related reactions as needed [see Warnings and Precautions (5.2) and Adverse Reactions (6.1)].
- Administer trimethoprim/sulfamethoxazole double strength (DS) twice daily 3 times per week (or equivalent) as Pneumocystis jirovecii pneumonia (PCP) prophylaxis.
- Administer famciclovir 250 mg BID or equivalent as herpetic prophylaxis.

Continue PCP and herpes viral prophylaxis for a minimum of 2 months after completion of CAMPATH or until the CD4+ count is ≥200 cells/µL, whichever occurs later [see Warnings and Precautions (5.3)].

2.3 Dosage Modification

- Withhold CAMPATH during serious infection or other serious adverse reactions until resolution.
- Discontinue CAMPATH for autoimmune anemia or autoimmune thrombocytopenia.
- There are no dose modifications recommended for lymphopenia.

Dose Modification for Neutropenia or Thrombocytopenia [see Warnings and Precautions (5.1)]
Hematologic Values | Dosage Modification [If the delay between dosing is ≥7 days, initiate therapy at CAMPATH 3 mg and escalate to 10 mg and then to 30 mg as tolerated [see Dosage and Administration (2.1)].]
ANC <250/μL and/or platelet count ≤25,000/μL
For first occurrence: | Withhold CAMPATH therapy. Resume CAMPATH at 30 mg when ANC ≥500/μL and platelet count ≥50,000/μL.
For second occurrence: | Withhold CAMPATH therapy. Resume CAMPATH at 10 mg when ANC ≥500/μL and platelet count ≥50,000/μL.
For third occurrence: | Discontinue CAMPATH therapy.
≥50% decrease from baseline in patients initiating therapy with a baseline ANC ≤250/μL and/or a baseline platelet count ≤25,000/μL
For first occurrence: | Withhold CAMPATH therapy. Resume CAMPATH at 30 mg upon return to baseline value(s).
For second occurrence: | Withhold CAMPATH therapy. Resume CAMPATH at 10 mg upon return to baseline value(s).
For third occurrence: | Discontinue CAMPATH therapy.

2.4 Preparation and Administration

Parenteral drug products should be inspected visually for particulate matter and discoloration prior to administration. If particulate matter is present or the solution is discolored, discard the vial. DO NOT SHAKE VIAL.

Use aseptic technique during the preparation and administration of CAMPATH. Withdraw the necessary amount of CAMPATH from the vial into a syringe.

- To prepare the 3 mg dose, withdraw 0.1 mL into a 1 mL syringe calibrated in increments of 0.01 mL.
- To prepare the 10 mg dose, withdraw 0.33 mL into a 1 mL syringe calibrated in increments of 0.01 mL.
- To prepare the 30 mg dose, withdraw 1 mL in either a 1 mL or 3 mL syringe calibrated in 0.1 mL increments.

Inject syringe contents into 100 mL sterile 0.9% Sodium Chloride USP or 5% Dextrose in Water USP. Gently invert the bag to mix the solution. Discard syringe.

The vial contains no preservatives and is intended for single use only. DISCARD VIAL including any unused portion after withdrawal of dose.

Use within 8 hours after dilution. Store diluted CAMPATH at room temperature between 15°C to 30°C (59°F to 86°F) or refrigerated at 2°C to 8°C (36°F to 46°F). Protect from light.

2.5 Incompatibilities

CAMPATH is compatible with polyvinylchloride (PVC) bags and PVC or polyethylene-lined PVC administration sets. Do not add or simultaneously infuse other drug substances through the same intravenous line.

3 DOSAGE FORMS AND STRENGTHS

Injection: 30 mg/1 mL as a clear, colorless solution in single-dose vial

4 CONTRAINDICATIONS

None.

5 WARNINGS AND PRECAUTIONS

5.1 Cytopenias

Severe, including fatal, autoimmune anemia and thrombocytopenia, and prolonged myelosuppression have been reported in patients receiving CAMPATH.

In addition, hemolytic anemia, pure red cell aplasia, bone marrow aplasia, and hypoplasia have been reported after treatment with CAMPATH at the recommended dose. Single doses of CAMPATH greater than 30 mg or cumulative doses greater than 90 mg per week increase the incidence of pancytopenia.

Withhold CAMPATH for severe cytopenias (except lymphopenia). Discontinue for autoimmune cytopenias or recurrent/persistent severe cytopenias (except lymphopenia) [see Dosage and Administration (2.3)]. No data exist on the safety of CAMPATH resumption in patients with autoimmune cytopenias or marrow aplasia [see Adverse Reactions (6.1)].

Obtain complete blood counts (CBC) at weekly intervals during CAMPATH therapy and more frequently if worsening anemia, neutropenia, or thrombocytopenia occurs. Assess CD4+ counts after treatment until recovery to ≥200 cells/µL [see Dosage and Administration (2.3) and Adverse Reactions (6)].

5.2 Infusion-Related Reactions

Adverse reactions occurring during or shortly after CAMPATH infusion include pyrexia, chills/rigors, nausea, hypotension, urticaria, dyspnea, rash, emesis, and bronchospasm [see Adverse Reactions (6.1)]. In clinical trials, the frequency of infusion-related reactions was highest in the first week of treatment. Monitor for the signs and symptoms listed above and withhold infusion for Grade 3 or 4 infusion-related reactions.

The following serious, including fatal, infusion-related reactions have been identified in postmarketing reports: syncope, pulmonary infiltrates, acute respiratory distress syndrome (ARDS), respiratory arrest, cardiac arrhythmias, myocardial infarction, acute cardiac insufficiency, cardiac arrest, angioedema, and anaphylactoid shock.

Initiate CAMPATH according to the recommended dose-escalation scheme [see Dosage and Administration (2.1)]. Premedicate patients with an antihistamine and acetaminophen prior to each dose. Institute appropriate medical management (e.g., glucocorticoids, epinephrine, meperidine) for infusion-related reactions as needed [see Dosage and Administration (2.2)]. If therapy is interrupted for 7 or more days, reinstitute CAMPATH with gradual dose escalation [see Dosage and Administration (2.1)].

5.3 Immunosuppression/Infections

CAMPATH treatment results in severe and prolonged lymphopenia with a concomitant increased incidence of opportunistic infections [see Adverse Reactions (6.1)]. Administer PCP and herpes viral prophylaxis during treatment with CAMPATH and for a minimum of 2 months after completion of CAMPATH or until the CD4+ count is ≥200 cells/µL, whichever occurs later [see Dosage and Administration (2.2)]. Prophylaxis does not eliminate these infections.

Routinely monitor patients for CMV infection during treatment with CAMPATH and for at least 2 months following completion of CAMPATH. Withhold CAMPATH for serious infections and during antiviral treatment for CMV infection or confirmed CMV viremia (defined as polymerase chain reaction [PCR] positive CMV in ≥2 consecutive samples obtained 1 week apart). Initiate therapeutic ganciclovir (or equivalent) for CMV infection or confirmed CMV viremia.

Epstein-Barr virus (EBV) infection, including severe and fatal EBV-associated hepatitis, has been reported in patients who received CAMPATH.

Monitor for sign and symptoms of EBV infections. Withhold CAMPATH for EBV reactivation or severe infection.

Administer only irradiated blood products to avoid transfusion associated Graft versus Host Disease (TAGVHD), unless emergent circumstances dictate immediate transfusion.

In patients who received CAMPATH as initial therapy, recovery of CD4+ counts to ≥200 cells/µL occurred by 6 months following completion of CAMPATH; however, at 2 months post treatment, the median was 183 cells/µL. In previously treated patients who received CAMPATH, the median time to recovery of CD4+ counts to ≥200 cells/µL was 2 months; however, full recovery (to baseline) of CD4+ and CD8+ counts may take more than 12 months [see Adverse Reactions (6)].

5.4 Immunization

The safety of immunization with live viral vaccines following CAMPATH therapy has not been studied. Do not administer live viral vaccines to patients or infants born to patients receiving CAMPATH. The ability to generate an immune response to any vaccine following CAMPATH therapy has not been studied.

6 ADVERSE REACTIONS

The following clinically significant adverse reactions are discussed in greater detail in other sections of the label:

- Cytopenias [see Warnings and Precautions (5.1)]
- Infusion-Related Reactions [see Warnings and Precautions (5.2)]
- Immunosuppression/Infections [see Warnings and Precautions (5.3)]

6.1 Clinical Trials Experience

Because clinical trials are conducted under widely varying conditions, adverse reaction rates observed in the clinical trials of a drug cannot be directly compared to rates in the clinical trials of another drug and may not reflect the rates observed in practice.

The data below reflect exposure to CAMPATH in 296 patients with CLL of whom 147 were previously untreated and 149 received at least 2 prior chemotherapy regimens. The median duration of exposure was 11.7 weeks for previously untreated patients and 8 weeks for previously treated patients.

The most common adverse reactions with CAMPATH are: infusion-related reactions (pyrexia, chills, hypotension, urticaria, nausea, rash, tachycardia, dyspnea), cytopenias (neutropenia, lymphopenia, thrombocytopenia, anemia), infections (CMV viremia, CMV infection, other infections), gastrointestinal symptoms (nausea, emesis, abdominal pain), and neurological symptoms (insomnia, anxiety). The most common serious adverse reactions are cytopenias, infusion-related reactions, and immunosuppression/infections.

Lymphopenia

Severe lymphopenia and a rapid and sustained decrease in lymphocyte subsets occurred in previously untreated and previously treated patients following administration of CAMPATH. In previously untreated patients, the median CD4+ was 0 cells/μL at one month after treatment and 238 cells/μL [25%–75% interquartile range 115 to 418 cells/μL at 6 months post treatment [see Warnings and Precautions (5.3)].

Neutropenia

In previously untreated patients, the incidence of Grade 3 or 4 neutropenia was 42% with a median time to onset of 31 days and a median duration of 37 days. In previously treated patients, the incidence of Grade 3 or 4 neutropenia was 64% with a median duration of 28 days. Ten percent of previously untreated patients and 17% of previously treated patients received granulocyte colony stimulating factors.

Anemia

In previously untreated patients, the incidence of Grade 3 or 4 anemia was 12% with a median time to onset of 31 days and a median duration of 8 days. In previously treated patients, the incidence of Grade 3 or 4 anemia was 38%. Seventeen percent of previously untreated patients and 66% of previously treated patients received either erythropoiesis stimulating agents, transfusions or both.

Thrombocytopenia

In previously untreated patients, the incidence of Grade 3 or 4 thrombocytopenia was 14% with a median time to onset of 9 days and a median duration of 14 days. In previously treated patients, the incidence of Grade 3 or 4 thrombocytopenia was 52% with a median duration of 21 days. Autoimmune thrombocytopenia was reported in 2% of previously treated patients with one fatality.

Infusion-Related Reactions

Infusion-related reactions, which included pyrexia, chills, hypotension, urticaria, and dyspnea, were common. Grade 3 and 4 pyrexia and/or chills occurred in approximately 10% of previously untreated patients and in approximately 35% of previously treated patients. The occurrence of infusion-related reactions was greatest during the initial week of treatment and decreased with subsequent doses of CAMPATH. All patients were pretreated with antipyretics and antihistamines; additionally, 43% of previously untreated patients received glucocorticoid pre-treatment.

Infections

In the study of previously untreated patients, patients were tested weekly for CMV using a PCR assay from initiation through completion of therapy, and every 2 weeks for the first 2 months following therapy. CMV infection occurred in 16% (23/147) of previously untreated patients; approximately one-third of these infections were serious or life threatening. In studies of previously treated patients in which routine CMV surveillance was not required, CMV infection was documented in 6% (9/149) of patients; nearly all of these infections were serious or life threatening.

Other infections were reported in approximately 50% of patients across all studies. Grade 3 to 5 sepsis ranged from 3% to 10% across studies and was higher in previously treated patients. Grade 3 to 4 febrile neutropenia ranged from 5% to 10% across studies and was higher in previously treated patients. Infection-related fatalities occurred in 2% of previously untreated patients and 16% of previously treated patients. There were 198 episodes of other infection in 109 previously untreated patients; 16% were bacterial, 7% were fungal, 4% were other viral, and in 73% the organism was not identified.

Cardiac

Cardiac dysrhythmias occurred in approximately 14% of previously untreated patients. The majority were tachycardias and were temporally associated with infusion; dysrhythmias were Grade 3 or 4 in 1% of patients.

Previously Untreated Patients

Table 1 contains selected adverse reactions observed in 294 patients randomized (1:1) to receive CAMPATH or chlorambucil as first line therapy for B-CLL. CAMPATH was administered at a dose of 30 mg intravenously three times weekly for up to 12 weeks. The median duration of therapy was 11.7 weeks with a median weekly dose of 82 mg (25%–75% interquartile range: 69–90 mg).

Table 1: Per Patient Incidence of Selected [Adverse reactions occurring at a higher relative frequency in the CAMPATH arm] Adverse Reactions in Treatment Naive B-CLL Patients
 |  | CAMPATH (n=147) |  | Chlorambucil (n=147)
 |  | All Grades [NCI CTC version 2.0 for adverse reactions; NCI CTCAE version 3.0 for laboratory values] % | Grades 3–4 % | All Grades % | Grades 3–4 %
Blood and Lymphatic System Disorders | Lymphopenia | 97 | 97 | 9 | 1
Blood and Lymphatic System Disorders | Neutropenia | 77 | 42 | 51 | 26
Blood and Lymphatic System Disorders | Anemia | 76 | 13 | 54 | 18
Blood and Lymphatic System Disorders | Thrombocytopenia | 71 | 13 | 70 | 14
General Disorders and Administration Site Conditions | Pyrexia | 69 | 10 | 11 | 1
General Disorders and Administration Site Conditions | Chills | 53 | 3 | 1 | 0
Infections and Infestations | CMV viremia [CMV viremia (without evidence of symptoms) includes both cases of single PCR positive test results and of confirmed CMV viremia (≥2 occasions in consecutive samples 1 week apart). For the latter, ganciclovir (or equivalent) was initiated per protocol.] | 55 | 4 | 8 | 0
Infections and Infestations | CMV infection | 16 | 5 | 0 | 0
Infections and Infestations | Other infections | 74 | 21 | 65 | 10
Skin and Subcutaneous Tissue Disorders | Urticaria | 16 | 2 | 1 | 0
Skin and Subcutaneous Tissue Disorders | Rash | 13 | 1 | 4 | 0
Skin and Subcutaneous Tissue Disorders | Erythema | 4 | 0 | 1 | 0
Vascular Disorders | Hypotension | 16 | 1 | 0 | 0
Vascular Disorders | Hypertension | 14 | 5 | 2 | 1
Nervous System Disorders | Headache | 14 | 1 | 8 | 0
Nervous System Disorders | Tremor | 3 | 0 | 1 | 0
Respiratory, Thoracic and Mediastinal Disorders | Dyspnea | 14 | 4 | 7 | 3
Gastrointestinal Disorders | Diarrhea | 10 | 1 | 4 | 0
Psychiatric Disorders | Insomnia | 10 | 0 | 3 | 0
Psychiatric Disorders | Anxiety | 8 | 0 | 1 | 0
Cardiac Disorders | Tachycardia | 10 | 0 | 1 | 0

Previously Treated Patients

Additional safety information was obtained from 3 single arm studies of 149 previously treated patients with CLL administered 30 mg CAMPATH intravenously three times weekly for 4 to 12 weeks (median cumulative dose 673 mg [range 2–1106 mg]; median duration of therapy 8.0 weeks). Adverse reactions in these studies not listed in Table 1 that occurred at an incidence rate of >5% were fatigue, nausea, emesis, musculoskeletal pain, anorexia, dysesthesia, mucositis, and bronchospasm.

6.2 Immunogenicity

As with all therapeutic proteins, there is potential for immunogenicity. The incidence of antibody formation is highly dependent on the sensitivity and specificity of the assay. Additionally, the observed incidence of antibody (including neutralizing antibody) positivity in an assay may be influenced by several factors including assay methodology, sample handling, timing of sample collection, concomitant medications, and underlying disease. For these reasons, comparison of the incidence of antibodies with the incidence of antibodies to other alemtuzumab products may be misleading.

Using an ELISA assay, anti-human antibodies (HAHA) were detected in 11 of 133 (8.3%) previously untreated patients. In addition, two patients were weakly positive for neutralizing activity. Limited data suggest that the anti-CAMPATH antibodies did not adversely affect tumor response. Four of 211 (1.9%) previously treated patients were found to have antibodies to CAMPATH following treatment.

6.3 Postmarketing Experience

CAMPATH

The following adverse reactions have been identified during postapproval use of CAMPATH. Because these reactions are reported voluntarily from a population of uncertain size, it is not always possible to reliably estimate their frequency or establish a causal relationship to drug exposure.

General Disorders and Administration Site Conditions: Fatal infusion-related reactions.

Cardiovascular Disorders: Congestive heart failure, cardiomyopathy, decreased ejection fraction (some patients had been previously treated with cardiotoxic agents).

Cerebrovascular Disorders: Cervicocephalic arterial dissection, stroke, including hemorrhagic and ischemic stroke.

Gastrointestinal Disorders: Acute acalculous cholecystitis.

Immune System Disorders: Goodpasture's syndrome, Graves' disease, aplastic anemia, Guillain-Barré syndrome, chronic inflammatory demyelinating polyradiculoneuropathy, serum sickness, fatal transfusion associated graft versus host disease, hemophagocytic lymphohistiocytosis (HLH).

Infections: Epstein-Barr virus (EBV) infection, progressive multifocal leukoencephalopathy (PML), reactivation of latent viruses.

Metabolism and Nutrition Disorders: Tumor lysis syndrome.

Neoplasms: EBV-associated lymphoproliferative disorder.

Nervous System Disorders: Optic neuropathy.

Renal and Urinary Disorders: Glomerular nephropathies.

Other Alemtuzumab Products

The following adverse reactions have been identified during postapproval use of another alemtuzumab product. Because these reactions are reported voluntarily from a population of uncertain size, it is not always possible to reliably estimate their frequency or establish a causal relationship to drug exposure.

Endocrine Disorders: Hypothyroidism, hyperthyroidism, and thyroiditis.

Nervous System Disorders: Autoimmune encephalitis.

7 DRUG INTERACTIONS

No formal drug interaction studies have been performed with CAMPATH.

8 USE IN SPECIFIC POPULATIONS

8.1 Pregnancy

Risk Summary

Based on findings from animal studies, CAMPATH may cause fetal harm when administered to a pregnant woman. Available data from published cohort studies in pregnant women are insufficient to establish a CAMPATH-associated risk of major birth defects, miscarriage or adverse maternal or fetal outcomes. Alemtuzumab was embryolethal in pregnant huCD52 transgenic mice when administered during organogenesis (see Data). Human IgG antibodies are known to cross the placental barrier; therefore, CAMPATH may be transmitted from the mother to the developing fetus. Advise women of the potential risk to the fetus. Infants born to pregnant women treated with CAMPATH may be at increased risk of infection (see Clinical Considerations).

The background risk of major birth defects and miscarriage for the indicated population is unknown. All pregnancies have a background risk of birth defect, loss, or other adverse outcomes. In the U.S. general population, the estimated background risk of major birth defects and miscarriage in clinically recognized pregnancies is 2% to 4% and 15% to 20%, respectively.

Clinical Considerations

Fetal/Neonatal adverse reactions

Monoclonal antibodies are transported across the placenta as pregnancy progresses, with the largest amount transferred during the third trimester. Consider the risks and benefits of administering live or live-attenuated vaccines to infants exposed to CAMPATH in utero [see Warnings and Precautions (5.3, 5.4)].

Data

Animal data

When alemtuzumab was administered to pregnant huCD52 transgenic mice during organogenesis (gestation days [GD] 6–10 or GD 11–15) at intravenous doses of 3 or 10 mg/kg, no teratogenic effects were observed. However, there was an increase in embryolethality (increased postimplantation loss and the number of dams with all fetuses dead or resorbed) in pregnant animals dosed during GD 11–15. In a separate study in pregnant huCD52 transgenic mice, administration of alemtuzumab during organogenesis (GD 6–10 or GD 11–15) at intravenous doses of 3 or 10 mg/kg, decreases in B-lymphocyte and T-lymphocyte populations were observed in the offspring at both doses tested.

In pregnant huCD52 transgenic mice administered alemtuzumab at intravenous doses of 3 or 10 mg/kg/day throughout gestation and lactation, there was an increase in pup deaths during the lactation period at 10 mg/kg. Decreases in T-lymphocyte and B-lymphocyte populations and in antibody response were observed in offspring at both doses tested.

8.2 Lactation

Risk Summary

There are no data on the presence of alemtuzumab in human milk, effects on milk production, or the breastfed child. The effects of local gastrointestinal exposure and limited systemic exposure in the breastfed infant to alemtuzumab are unknown. Alemtuzumab was detected in the milk of lactating huCD52 transgenic mice administered alemtuzumab (see Data). Maternal IgG is known to be present in human milk and when a drug is present in animal milk, it is likely that the drug will be present in human milk.

Because of the potential for serious adverse reactions from CAMPATH in a breastfed child, including reduced lymphocyte counts, advise lactating women not to breastfeed during treatment with CAMPATH and for at least 3 months following the last dose.

Data

Alemtuzumab was detected in the milk of lactating huCD52 transgenic mice following intravenous administration of alemtuzumab at a dose of 10 mg/kg on postpartum days 8–12. Serum levels of alemtuzumab were similar in lactating mice and offspring on postpartum day 13 and were associated with evidence of pharmacological activity (decrease in lymphocyte counts) in the offspring.

8.3 Females and Males of Reproductive Potential

CAMPATH may cause embryo-fetal harm when administered to pregnant women [see Use in Specific Populations (8.1)].

Pregnancy Testing

Pregnancy testing is recommended for females of reproductive potential prior to initiating CAMPATH therapy.

Contraception

Females

Advise female patients of reproductive potential to use effective contraception during treatment with CAMPATH and for at least 3 months after the last dose.

Infertility

Based on findings from animal studies, alemtuzumab may impair fertility in females and males of reproductive potential [see Nonclinical Toxicology (13.1)]. The reversibility of the effect on fertility is unknown.

8.4 Pediatric Use

Safety and effectiveness of CAMPATH have not been established in pediatric patients.

8.5 Geriatric Use

Of 147 previously untreated B-CLL patients treated with CAMPATH, 35% were ≥ age 65 and 4% were ≥ age 75. Of 149 previously treated patients with B-CLL, 44% were ≥65 years of age and 10% were ≥75 years of age. Clinical studies of CAMPATH did not include sufficient number of subjects age 65 and over to determine whether they respond differently than younger subjects. Other reported clinical experience has not identified differences in responses between the elderly and younger patients.

10 OVERDOSAGE

Across all clinical experience, the reported maximum single dose received was 90 mg. Bone marrow aplasia, infections, or severe infusion-related reactions occurred in patients who received a dose higher than recommended.

One patient who received an 80 mg dose intravenously experienced acute bronchospasm, cough, and dyspnea, followed by anuria and death. Another patient received two 90 mg doses intravenously one day apart during the second week of treatment and experienced a rapid onset of bone marrow aplasia.

There is no known specific antidote for CAMPATH overdosage. Discontinue CAMPATH and provide supportive therapy.

11 DESCRIPTION

Alemtuzumab, a CD52-directed cytolytic antibody, is a recombinant DNA-derived humanized monoclonal antibody (CAMPATH-1H). CAMPATH-1H is an IgG1 kappa antibody with human variable framework and constant regions, and complementarity-determining regions from a murine (rat) monoclonal antibody (CAMPATH-1G). The CAMPATH-1H antibody has an approximate molecular weight of 150 kD. CAMPATH is produced in mammalian cell (Chinese hamster ovary) suspension culture in a medium containing neomycin. Neomycin is not detectable in the final product.

CAMPATH (alemtuzumab) injection is a sterile, clear, colorless, isotonic solution (pH 6.8–7.4) in a single-dose vial for intravenous use. Each single-dose vial of CAMPATH contains 30 mg alemtuzumab, 8.0 mg sodium chloride, 1.44 mg dibasic sodium phosphate, 0.2 mg potassium chloride, 0.2 mg monobasic potassium phosphate, 0.1 mg polysorbate 80, and 0.0187 mg disodium edetate dihydrate. No preservatives are added.

12 CLINICAL PHARMACOLOGY

12.1 Mechanism of Action

CAMPATH binds to CD52, an antigen present on the surface of B and T lymphocytes, a majority of monocytes, macrophages, NK cells, and a subpopulation of granulocytes. A proportion of bone marrow cells, including some CD34+ cells, express variable levels of CD52. The proposed mechanism of action is antibody-dependent cellular-mediated lysis following cell surface binding of CAMPATH to the leukemic cells.

12.2 Pharmacodynamics

Cardiac Electrophysiology

The effect of multiple doses of alemtuzumab (12 mg/day for 5 days) on the QTc interval was evaluated in a single-arm study in 53 patients without malignancy. No large changes in the mean QTc interval (i.e., >20 ms) were detected in the study. A mean increase in heart rate of 22 to 26 beats/min was observed for at least 2 hours following the initial infusion of alemtuzumab. This increase in heart rate was not observed with subsequent doses.

12.3 Pharmacokinetics

CAMPATH pharmacokinetics were characterized in a study of 30 previously treated B-CLL patients in whom CAMPATH was administered at the recommended dose and schedule. After 12 weeks of dosing, patients exhibited a 7-fold increase in mean AUC.

Distribution

After the last 30 mg dose, the mean volume of distribution at steady-state was 0.18 L/kg (range 0.1 to 0.4 L/kg).

Elimination

CAMPATH pharmacokinetics displayed nonlinear elimination kinetics. Systemic clearance decreased with repeated administration due to decreased receptor-mediated clearance (i.e., loss of CD52 receptors in the periphery). Mean half-life was 11 hours (range 2 to 32 hours) after the first 30 mg dose and was 6 days (range 1 to 14 days) after the last 30 mg dose.

Specific Populations

The effects of renal or hepatic impairment on the pharmacokinetics of CAMPATH have not been studied.

13 NONCLINICAL TOXICOLOGY

13.1 Carcinogenesis, Mutagenesis, Impairment of Fertility

Studies to assess the carcinogenic or genotoxic potential of CAMPATH have not been conducted.

In fertility studies, alemtuzumab (3 or 10 mg/kg intravenously) was administered to huCD52 transgenic male mice on 5 consecutive days prior to cohabitation with untreated wild-type females. No effect on fertility or reproductive performance was observed. However, adverse effects on sperm parameters (including abnormal morphology [detached/no head] and reduced total count and motility) were observed at both doses tested.

When alemtuzumab (3 or 10 mg/kg intravenously) was administered to huCD52 transgenic female mice for 5 consecutive days prior to cohabitation with untreated wild-type males, there was a decrease in the average number of corpora lutea and implantation sites and an increase in postimplantation loss, resulting in fewer viable embryos at the higher dose tested.

14 CLINICAL STUDIES

14.1 Previously Untreated B-CLL Patients

CAMPATH was evaluated in an open-label, randomized (1:1) active-controlled study in previously untreated patients with B-CLL, Rai Stage I–IV, with evidence of progressive disease requiring therapy. Patients received either CAMPATH 30 mg intravenously 3 times per week for a maximum of 12 weeks or chlorambucil 40 mg/m^2 orally once every 28 days for a maximum of 12 cycles.

Of the 297 patients randomized, the median age was 60 years, 72% were male, 99% were Caucasian, 96% had a WHO performance status 0–1, 23% had maximum lymph node diameter ≥5 cm, 34% were Rai Stage III/IV, and 8% were treated in the U.S.

Patients randomized to receive CAMPATH experienced longer progression free survival (PFS) compared to those randomized to receive chlorambucil (median PFS 14.6 months vs. 11.7 months, respectively). The overall response rates were 83% and 55% (p <0.0001) and the complete response rates were 24% and 2% (p <0.0001) for CAMPATH and chlorambucil arms, respectively. The Kaplan-Meier curve for PFS is shown in Figure 1.

Figure 1: Progression Free Survival in Previously Untreated B-CLL Patients [Log-rank test adjusted for Rai Stage (I–II vs. III–IV).]

14.2 Previously Treated B-CLL Patients

CAMPATH was evaluated in three multicenter, open-label, single-arm studies of 149 patients with B-CLL previously treated with alkylating agents, fludarabine, or other chemotherapies. Patients were treated with the recommended dose of CAMPATH 30 mg intravenously 3 times per week for up to 12 weeks. Partial response rates of 21% to 31% and complete response rates of 0% to 2% were observed.

16 HOW SUPPLIED/STORAGE AND HANDLING

CAMPATH (alemtuzumab) is supplied in clear glass single-dose vial containing 30 mg of alemtuzumab in 1 mL of solution. Each carton contains three CAMPATH vials (NDC 58468-0357-3) or one CAMPATH vial (NDC 58468-0357-1).

STORAGE AND HANDLING

Store CAMPATH at 2°C to 8°C (36°F to 46°F). Do not freeze. If accidentally frozen, thaw at 2°C to 8°C before administration. Protect from direct sunlight.

17 PATIENT COUNSELING INFORMATION

Cytopenias

Advise patients to report any signs or symptoms such as bleeding, easy bruising, petechiae or purpura, pallor, weakness or fatigue [see Warnings and Precautions (5.1) and Adverse Reactions (6.1)].

Infusion-Related Reactions

Advise patients of the signs and symptoms of infusion-related reactions and of the need to take premedications as prescribed [see Warnings and Precautions (5.2) and Adverse Reactions (6.1)].

Immunosuppression/Infections

Advise patients to immediately report symptoms of infection (e.g., pyrexia) and to take prophylactic anti-infectives for PCP (trimethoprim/sulfamethoxazole DS or equivalent) and for herpes virus (famciclovir or equivalent) as prescribed [see Warnings and Precautions (5.3) and Adverse Reactions (6.1)].

Advise patients that irradiation of blood products is required [see Warnings and Precautions (5.3)].

Immunization

Advise patients that they should not be immunized with live viral vaccines if they have recently been treated with CAMPATH. Advise females with infants exposed to CAMPATH in utero to inform the pediatrician of the exposure [see Warnings and Precautions (5.4)].

Embryo-Fetal Toxicity

Advise pregnant women and females of reproductive potential of the potential risk to a fetus. Advise females to inform their healthcare provider of a known or suspected pregnancy [see Use in Specific Populations (8.1, 8.3)].

Advise female patients of reproductive potential to use effective contraception during treatment with CAMPATH and for 3 months after the final dose [see Use in Specific Populations (8.1, 8.3)].

Lactation

Advise females not to breastfeed during treatment with CAMPATH and for 3 months after the final dose [see Use in Specific Populations (8.2)].

Infertility

Advise females and males of reproductive potential that CAMPATH may impair fertility [see Use in Specific Populations (8.3) and Nonclinical Toxicology (13.1)].

Glomerular Nephropathies

Advise patients on signs and symptoms of glomerular nephropathies that may occur months to years after receiving CAMPATH [see Adverse Reactions (6.2)].

Manufactured and distributed by:
Genzyme Corporation, Cambridge, MA 02141
A SANOFI COMPANY
US License Number: 1596

CAMPATH is a registered trademark of Genzyme Corporation.

©2023 Genzyme Corporation.

PRINCIPAL DISPLAY PANEL - 1 Vial Carton

NDC 58468-0357-1
Rx only

Campath®
alemtuzumab
Injection

30 mg/mL

For Intravenous Infusion After Dilution

Sterile – No U.S. Standard of Potency

One single-dose vial
Discard unused portion

sanofi

PRINCIPAL DISPLAY PANEL - 3 Vial Carton

NDC 58468-0357-3
Rx only

Campath®
alemtuzumab
Injection

30 mg/mL

For Intravenous Infusion After Dilution

Sterile – No U.S. Standard of Potency

Three single-dose vials
Discard unused portion

sanofi